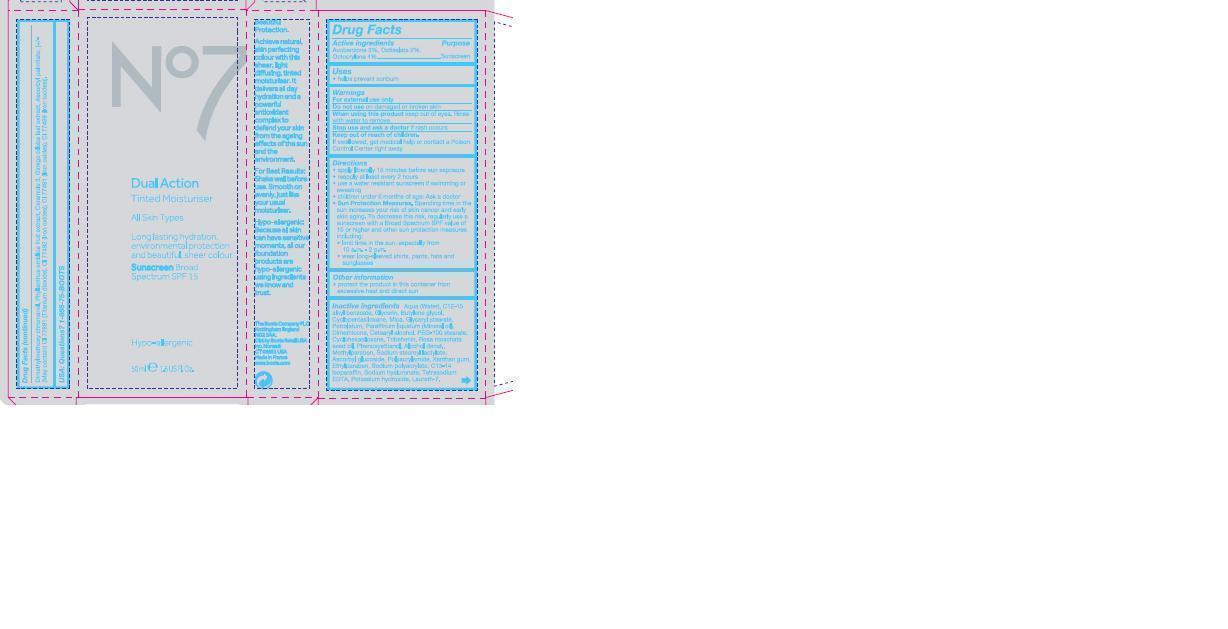 DRUG LABEL: No7 Dual Action Tinted Moisturiser Medium
NDC: 61589-1913 | Form: EMULSION
Manufacturer: BCM Cosmetique SAS
Category: otc | Type: HUMAN OTC DRUG LABEL
Date: 20191220

ACTIVE INGREDIENTS: AVOBENZONE 1.5 g/50 g; OCTISALATE 1 g/50 g; OCTOCRYLENE 2 g/50 g
INACTIVE INGREDIENTS: WATER; ALKYL (C12-15) BENZOATE; GLYCERIN; BUTYLENE GLYCOL; CYCLOMETHICONE 5; MICA; GLYCERYL MONOSTEARATE; PETROLATUM; MINERAL OIL; DIMETHICONE; CETOSTEARYL ALCOHOL; PEG-100 STEARATE; CYCLOMETHICONE 6; TRIBEHENIN; ROSA MOSCHATA SEED OIL; PHENOXYETHANOL; METHYLPARABEN; SODIUM STEAROYL LACTYLATE; ASCORBYL GLUCOSIDE; POLYACRYLAMIDE (1300000 MW); XANTHAN GUM; ETHYLPARABEN; SODIUM POLYACRYLATE (8000 MW); C13-14 ISOPARAFFIN; HYALURONATE SODIUM; EDETATE SODIUM TETRAHYDRATE; POTASSIUM HYDROXIDE; LAURETH-7; PHYLLANTHUS EMBLICA FRUIT JUICE; CERAMIDE 3; GINKGO BILOBA LEAF OIL; ASCORBYL PALMITATE; TITANIUM DIOXIDE; FERRIC OXIDE RED; FERRIC OXIDE YELLOW; FERRIC FERROCYANIDE

Tinted Moisturiser

active ingredients

Drug Facts

Active Ingredients Avobenzone 3%, Octisalate 2%, Octocrylene 4%

Purpose Sunscreen

Purpose section

Uses

helps prevent sunburn

Warnings.

For external use only

Do not use on damaged or broken skin

When using this product keep out of eyes. Rinse wither water to remove.

Ask Doctor.

Stop use and ask a doctor if rash occurs.

Keep out of reach of children. If swallowed, get medical help or contact a Poison Control Center right away.

Indications.

Directions

apply liberally 15 minutes bfore sun exposure

reapply at least every 2 hours.

use a water resistant sunscreen if swimming or sweating.

children under 6 months of age: Ask a doctor.

Sun Protection Measures.

Spending time in the sun increases your risk of skin cancer and early skin aging. To decrease this risk, regularly use a sunscreen with a Broad Spectrum SPF value of 15 or higher and other sun protection measures including:

limit time in the sun, especially from 10 a.m.–2 p.m.

wear long-sleeved shirts, pants, hats, and sunglasses.

Storage.

Other information

protect the product in this ocntainer from excessive heat and direct sun.

Inactives.

Inactive ingredients

Aqua (Water), C12-15 alkyl benzoate, Glycerin, Butylene glycol, Cyclopentasiloxane, Mica, Glyceryl stearate, Petrolatum, Paraffinum liquidum (Mineral oil), Dimethicone, Cetearyl alcohol, PEG-100 stearate, Cyclohexasiloxane, Tribehenin, Rosa moschata seed oil, Phenoxyethanol, Alcohol denat., Methylparaben, Sodium stearoyl lactylate, Ascorbyl glucoside, Polacrylamide, Xanthan gum, Ethylparaben, Sodium polacrylate, C13-14 iosparaffin, Sodium hyaluronate, Tetrasodium ETA, Potassium hydroxide, Laureth-7, Dimethylmethoxy chromanol, Phyllanthus emblica fruit extract, Ceramide 3, Ginkgo biloba leaf extract, Ascorbyl palmitate, (+/- (May contain) CI 77891 (Titanium dioxide), CI 77492 (Iron oxides), CI 77491 (Iron oxides), CI 77499 (Iron oxides).

Questions.

USA: Questions? 1-866-75-BOOTS.

Description.

Beautiful Protection.

Achieve natural, skin perfecting colour with this sheer, light diffusing, tinted moisturiser. It delivers all day hydration and a powerful antioxidant complex to defend your skin from the ageing effects of the sun and the environment.

For Best Results: Shake well before use. Smooth on evenly, just like your usual moisturiser.

Hypo-allergenic: Because all skin can have sensitive moments, all our foundation products are hypo-allergenic using ingredients we know and trust.

Information for patients.

The Boots Company PLC Nottingham England NG2 3AA

Dist by Boots Retail USA Inc Norwalk CT 06851 USA

Made in France

www.boots.com.

Jar front and active ingredients.

No7 Dual Action Tinted Moisturiser Sunscreen Broad Spectrum SPF 15

All skin types

Long lasting hydration, environmental protection and beautiful sheer colour

Hypo-allergenic

50ml 1.6 US Fl Oz

Active ingredients: Avobenzone 3%, Octisalate 2%, Octocrylene 4%.

Warnings.

Warning: Avoid contact with eyes. If product gets into the eyes rinse well with water immediately.

Description.

Beautiful Protection.

Achieve natural, skin perfecting colour with this sheer, light diffusing tinted moisturiser. It delivers all day hydrtion and a powerful antioxidant complex to defend your skin from the ageing effects of the sun and the environment.

For Best Results: Shake well before use. Smooth on evenly, just like your usual moisturiser.

Information for patients.

The Boots Company PLC Nottingham England NG2 3AA

Dist by Boots Retail USA Inc Norwalk CT 06851 USA

Made in France

www.boots.com.

Carton